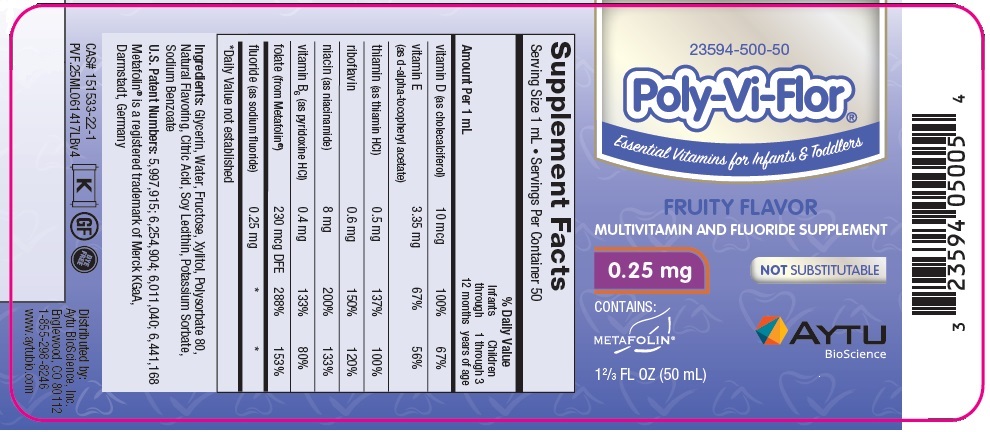 DRUG LABEL: Poly-Vi-Flor
NDC: 23594-500 | Form: SUSPENSION/ DROPS
Manufacturer: Aytu Therapeutics, LLC
Category: other | Type: DIETARY SUPPLEMENT
Date: 20210305

ACTIVE INGREDIENTS: CHOLECALCIFEROL 10 ug/1 mL; .ALPHA.-TOCOPHEROL ACETATE, D- 3.35 mg/1 mL; THIAMINE HYDROCHLORIDE 0.5 mg/1 mL; RIBOFLAVIN 0.6 mg/1 mL; NIACINAMIDE 8 mg/1 mL; PYRIDOXINE HYDROCHLORIDE 0.4 mg/1 mL; LEVOMEFOLATE CALCIUM 230 ug/1 mL; SODIUM FLUORIDE 0.25 mg/1 mL
INACTIVE INGREDIENTS: GLYCERIN; WATER; FRUCTOSE; XYLITOL; POLYSORBATE 80; CITRIC ACID MONOHYDRATE; LECITHIN, SOYBEAN; POTASSIUM SORBATE; SODIUM BENZOATE

HEALTH CLAIM

Multivitamin and Fluoride Supplement

Supplement Facts
Serving Size 1 mL • Servings Per Container 50
 |  | % Daily Value
Amount Per 1 mL |  | Infants through 12 months | Children 1 through 3 years of age
vitamin D (as cholecalciferol) | 10 mcg | 100% | 67%
vitamin E (as d-alpha-tocopheryl acetate) | 3.35 mg | 67% | 56%
thiamin (as thiamin HCl) | 0.5 mg | 137% | 100%
riboflavin | 0.6 mg | 150% | 120%
niacin (as niacinamide) | 8 mg | 200% | 133%
vitamin B6 (as pyridoxine HCl) | 0.4 mg | 133% | 80%
folate (from Metafolin®) | 230 mcg DFE | 288% | 153%
fluoride (as sodium fluoride) | 0.25 mg | * | *

*Daily Value not established

Ingredients: Glycerin, Water, Fructose, Xylitol, Polysorbate 80, Natural Flavoring, Citric Acid, Soy Lecithin, Potassium Sorbate, Sodium Benzoate

U.S. Patent Numbers: 5,997,915; 6,254,904; 6,011,040; 6,441,168

Metafolin® is a registered trademark of Merck KGaA, Darmstadt, Germany

Distributed by: Aytu BioScience, Inc.
Englewood, CO 80112
1-855-298-8246
www.aytubio.com

How to Use the Enclosed Dropper

Fill the dropper to the 1 mL line to provide the full daily dosage. Use full dosage, regardless of age or weight, unless your child's doctor recommends a different dosage. Dispense with a single squeeze.

Dosing Tips

Drops may be given by dispensing directly into the mouth. Drops may also be mixed with formula, fruit juice, cereal or other foods to increase your child's acceptance.

SAFE HANDLING WARNING

Shake well before use.

This product comes with a child-resistant cap. Refrigeration not required. After opening, store away from direct sunlight.

WARNING

As with all medicines, keep out of the reach of children.

PRINCIPAL DISPLAY PANEL - Poly-Vi-Flor with 0.25 mg of Fluoride

23594-500-50

Poly-Vi-Flor®

Essential Vitamins for Infants & Toddlers

FRUITY FLAVOR

MULTIVITAMIN AND FLUORIDE SUPPLEMENT

0.25 mg

NOT SUBSTITUTABLE

CONTAINS: METAFOLIN

1 2/3 FL OZ (50 mL)

AYTU BioScience